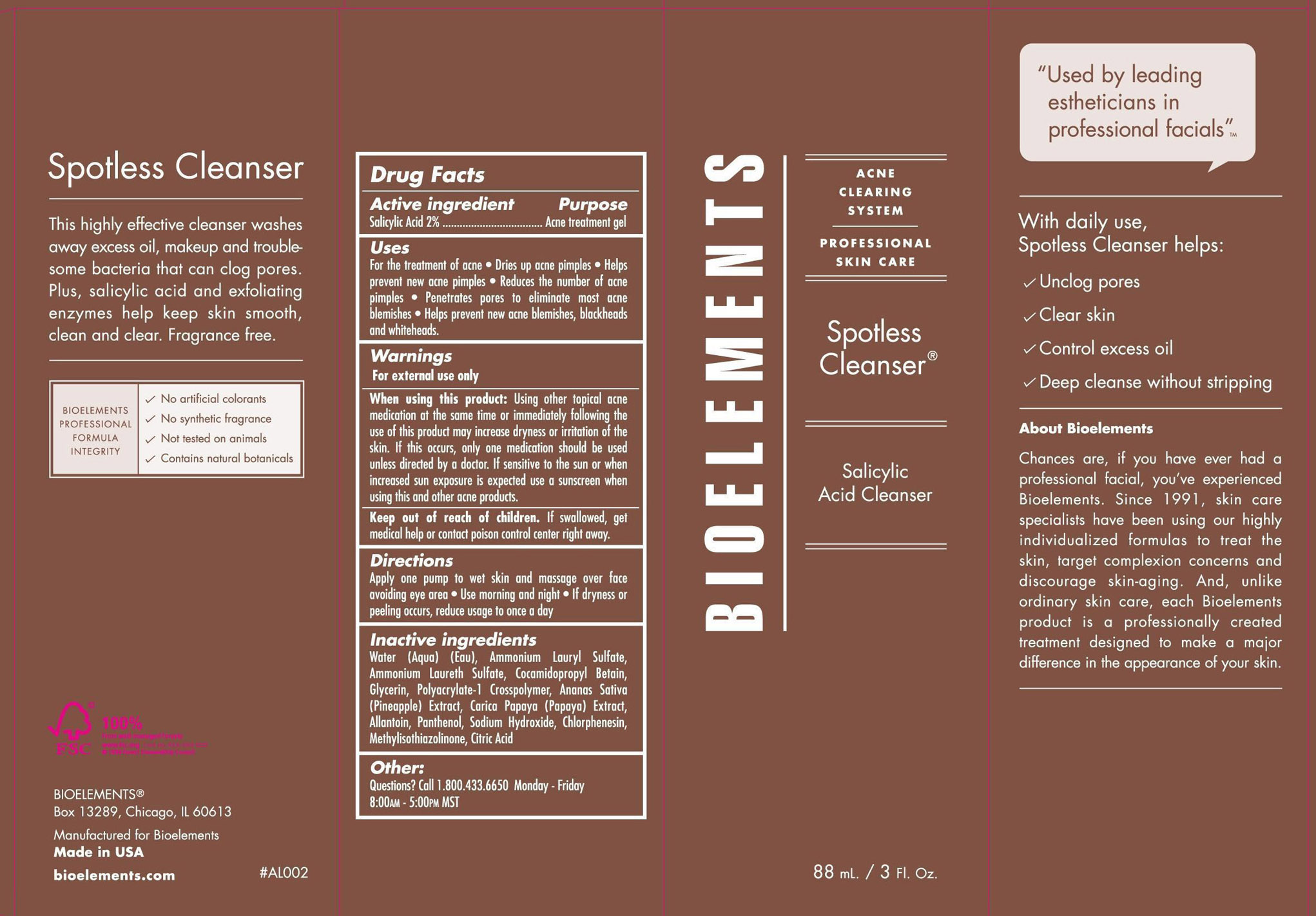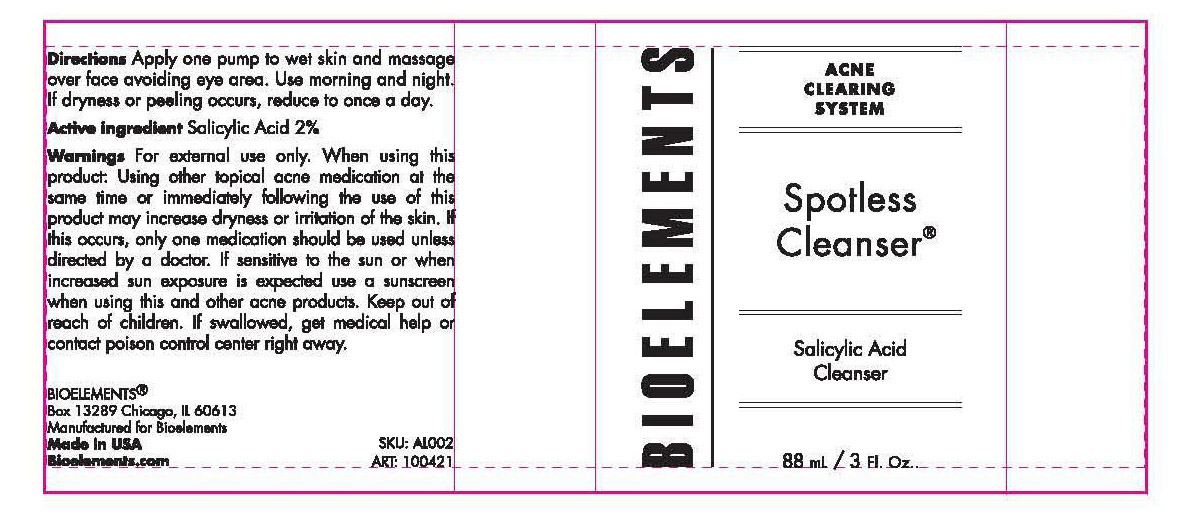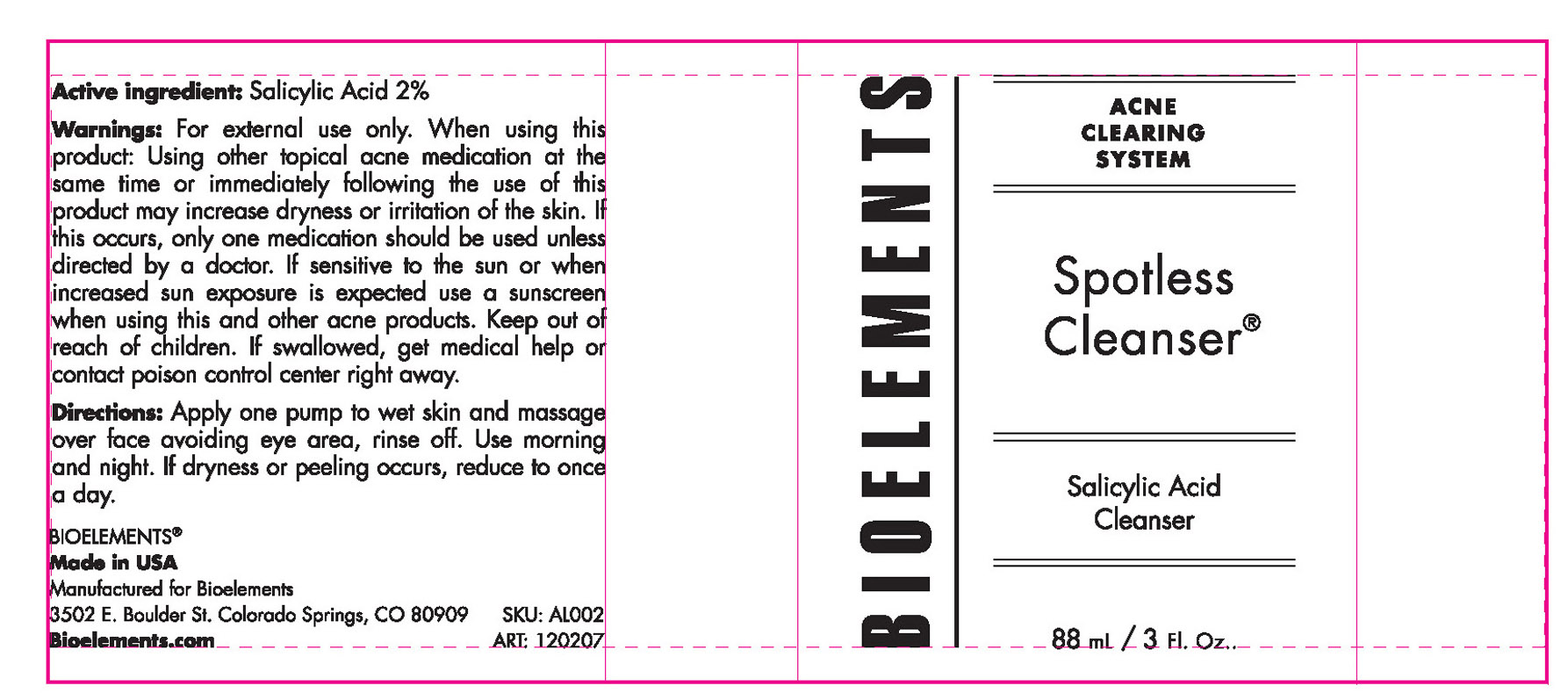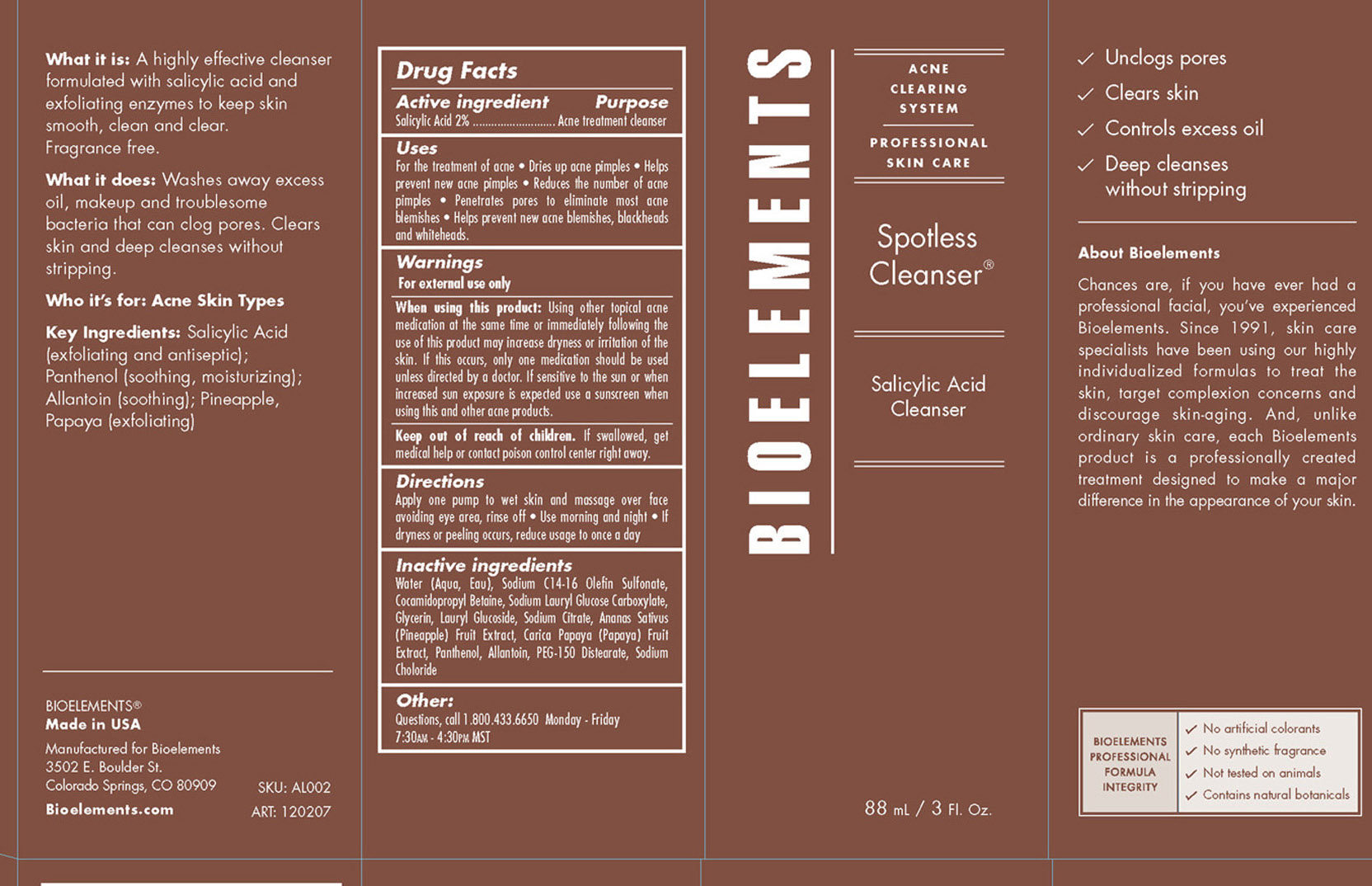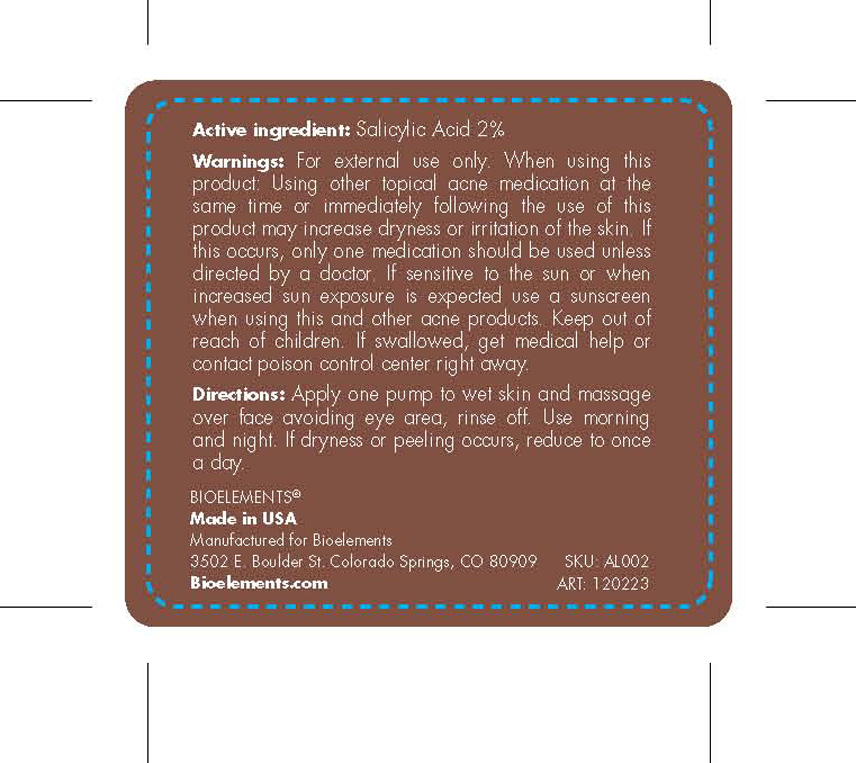 DRUG LABEL: Bioelements
NDC: 49825-113 | Form: GEL
Manufacturer: Bioelements Inc.
Category: otc | Type: HUMAN OTC DRUG LABEL
Date: 20120418

ACTIVE INGREDIENTS: SALICYLIC ACID 2 mL/100 mL
INACTIVE INGREDIENTS: WATER; SODIUM C14-16 OLEFIN SULFONATE; COCAMIDOPROPYL BETAINE; GLYCERIN; LAURYL GLUCOSIDE; SODIUM CITRATE; PINEAPPLE; PAPAYA; PANTHENOL; ALLANTOIN; PEG-150 DISTEARATE; SODIUM CHLORIDE

Spotless Cleanser

Active Ingredient Purpose
Salicylic Acid 2% Acne treatment gel

PURPOSE

-For the treatment of acne
-Dries up acne pimples
-Helps prevent new acne pimples
-Reduces the number of acne pimples
-Penetrates pores to eliminate most acne blemishes
-Helps prevent new acne blemishes, blackheads and whiteheads.

Keep out of reach of children.

if swallowed, get medical help or contact poison control center right away

INDICATIONS AND USAGE

-For external use only

When using this product: using other topical acne medication at the same time or immediately following the use of this product may increase dryness or irritation of the skin. If this occurs, only one medication should be used unless directed by a doctor. If sensitive to the sun or when increased sun exposure is expected use a sunscreen when using this and other acne products.

DOSAGE AND ADMINISTRATION

-Apply one pump to wet skin and massage over face avoiding eye area
-Use morning and night
-If dryness or peeling occurs, reduce usage to once a day

INACTIVE INGREDIENT

Inactive Ingredients: Water (Aqua, Eau), Sodium C14-16 Olefin Sulfonate, Cocamidopropyl Betaine, Sodium Lauryl Glucose Carboxylate, Glycerin, Lauryl Glucoside, Sodium Citrate, Ananas Sativus (Pineapple) Fruit Extract, Carica Papaya (Papaya) Fruit Extract, Panthenol, Allantoin, PEG-150 Distearate, Sodium Chloride

PACKAGE LABEL

Bioelements
Acne Clearing System
Spotless Cleanser
88 mL / 3 Fl. Oz.